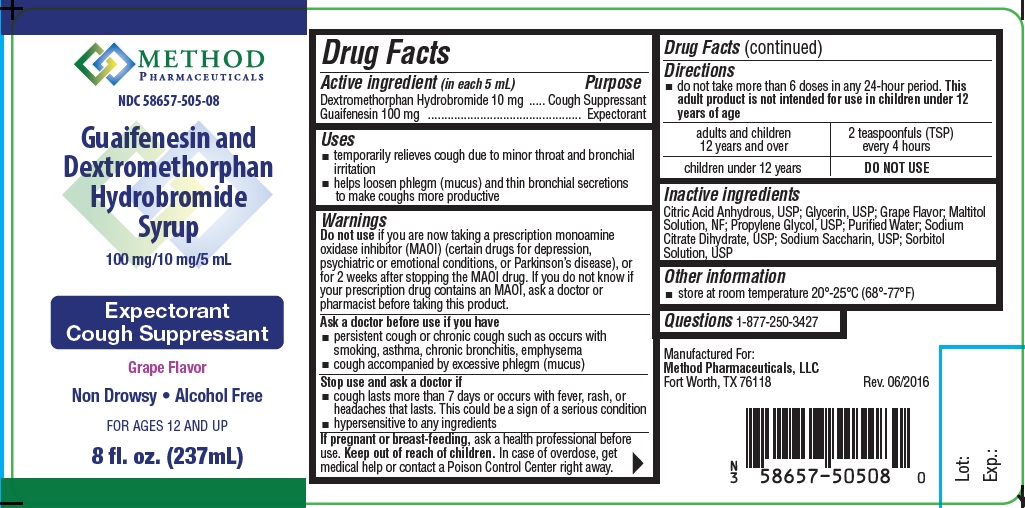 DRUG LABEL: Guaifenesin and Dextromethorphan Hydrobromide
NDC: 58657-505 | Form: SYRUP
Manufacturer: Method Pharmaceuticals
Category: otc | Type: HUMAN OTC DRUG LABEL
Date: 20251021

ACTIVE INGREDIENTS: DEXTROMETHORPHAN HYDROBROMIDE 10 mg/5 mL; GUAIFENESIN 100 mg/5 mL
INACTIVE INGREDIENTS: GLYCERIN; MALTITOL; SACCHARIN SODIUM; PROPYLENE GLYCOL; ANHYDROUS CITRIC ACID; TRISODIUM CITRATE DIHYDRATE; SORBITOL

Guaifenesin and Dextromethorphan Hydrobromide Syrup

Active ingredients

Dextromethorphan HBr, USP 10 mg
Guaifenesin, USP 100 mg

Purpose

Cough suppressant
Expectorant

Uses

- temporarily relieves cough due to minor throat and bronchial
  irritation
- helps loosen phlegm (mucus) and thin bronchial secretions
  to make coughs more productive

Warnings

Do not use if you are now taking a prescription
monoamine oxidase inhibitor (MAOI) (certain drugs
for depression, psychiatric or emotional conditions,
or Parkinson's disease), or for 2 weeks after
stopping the MAOI drug. If you do not know if
your prescription drug contains an MAOI, ask a
doctor or pharmacist before taking this product.

Ask a doctor before use if you have

- persistent cough or chronic cough such as occurs with smoking, asthma, chronic bronchitis, emphysema
- cough accompanied by excessive phlegm (mucus)

Stop use and ask a doctor if

- cough lasts more than 7 days or occurs with fever, rash, or
  headaches that lasts. This could be a sign of a serious condition
- hypersensitive to any ingredients

If pregnant or breast-feeding,

ask a health professional before use.

Keep out of reach of children.

In case of overdose, get medical help or contact a Poison Control Center right away.

Directions

- do not take more than 6 doses in any 24-hour period. This adult product is not intended for use in children under 12 years of age

adults and children 12 years and over | 2 teaspoonfuls (TSP) every 4 hours
children under 12 years | DO NOT USE

Inactive ingredients

Citric Acid Anhydrous, USP; Sodium Citrate Dihydrate, USP; Sodium Saccharin, USP; Propylene Glycol, USP; Grape Flavor; Sorbitol Solution, USP; Glycerin, USP; Maltitol Solution, NF

Other information

- store at room temperature 20°-25°C (68°-77°F)

Questions

1-877-250-3427

Principal Display Panel

Method Pharmaceuticals

NDC 58657-505-08

Guaifenesin and Dextromethorphan Hydrobromide Syrup

100 mg/10 mg/5 mL

Expectorant

Cough Suppressant

Grap Flavor

Non Drowsy • Alcohol Free

FOR AGES 12 AND UP

8 fl. oz. (237 mL)

Manufactured For:

Method Pharmaceuticals, LLC

Fort Worth, TX 76118 Rev. 06/2016